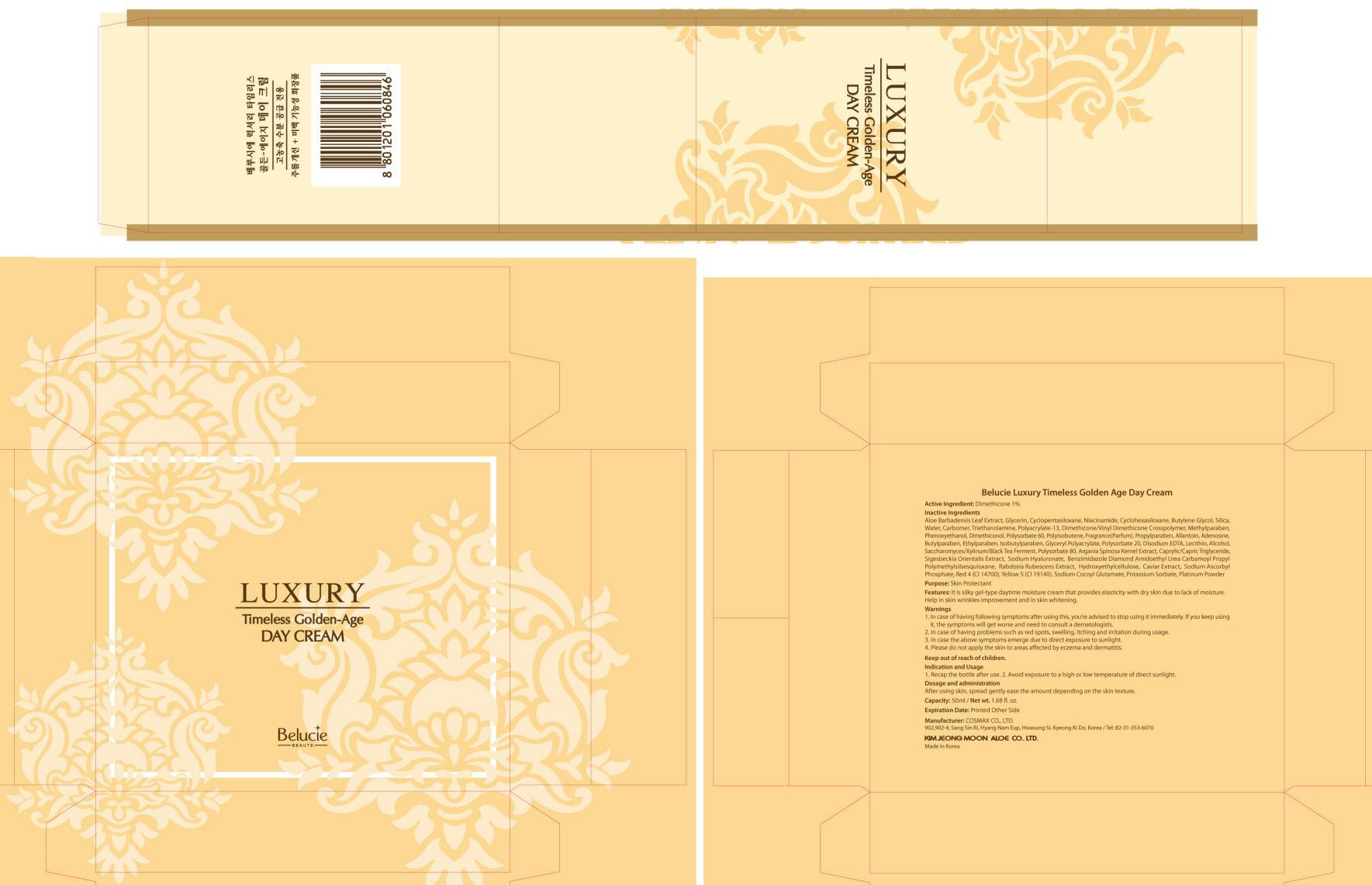 DRUG LABEL: Belucie Luxury Timeless Golden Age Day
NDC: 50410-060 | Form: CREAM
Manufacturer: KIMJEONGMOON ALOE CO., LTD.
Category: otc | Type: HUMAN OTC DRUG LABEL
Date: 20121130

ACTIVE INGREDIENTS: Dimethicone 0.5 g/50 mL
INACTIVE INGREDIENTS: ALOE VERA LEAF; Glycerin; Niacinamide; Butylene Glycol

ACTIVE INGREDIENT

Active Ingredient: Dimethicone 1%

INACTIVE INGREDIENT

Inactive Ingredients: Aloe Barbadensis Leaf Extract, Glycerin, Cyclopentasiloxane, Niacinamide, Cyclohexasiloxane, Butylene Glycol, Silica, Water, Carbomer, Triethanolamine, Polyacrylate-13, Dimethicone/Vinyl Dimethicone Crosspolymer, Methylparaben, Phenoxyethanol, Dimethiconol, Polysorbate 60, Polyisobutene, Fragrance(Parfum), Propylparaben, Allantoin, Adenosine, Butylparaben, Ethylparaben, Isobutylparaben, Glyceryl Polyacrylate, Polysorbate 20, Disodium EDTA, Lecithin, Alcohol, Saccharomyces/Xylinum/Black Tea Ferment, Polysorbate 80, Argania Spinosa Kernel Extract, Caprylic/Capric Triglyceride, Sigesbeckia Orientalis Extract, Sodium Hyaluronate, Benzimidazole Diamond Amidoethyl Urea Carbamoyl Propyl Polymethylsilsesquioxane, Rabdosia Rubescens Extract, Hydroxyethylcellulose, Caviar Extract, Sodium Ascorbyl Phosphate, Red 4 , Yellow 5, Sodium Cocoyl Glutamate, Potassium Sorbate, Platinum Powder

PURPOSE

Purpose: Skin Protectant

WARNINGS

1. In case of having following symptoms after using this, you’re advised to stop using it immediately. If you keep using it, the symptoms will get worse and need to consult a dematologists.
2. In case of having problems such as red spots, swelling, itching and irritation during usage
3. In case the above symptoms emerge due to direct exposure to sunlight
4. Please do not apply the skin to areas affected by eczema and dermatitis

KEEP OUT OF REACH OF CHILDREN

INDICATIONS AND USAGE

Indication and usage
1. Recap the bottle after use.
2. Avoid exposure to a high or low temperature of direct sunlight

DOSAGE AND ADMINISTRATION

After using skin, spread gently ease the amount depending on the skin texture